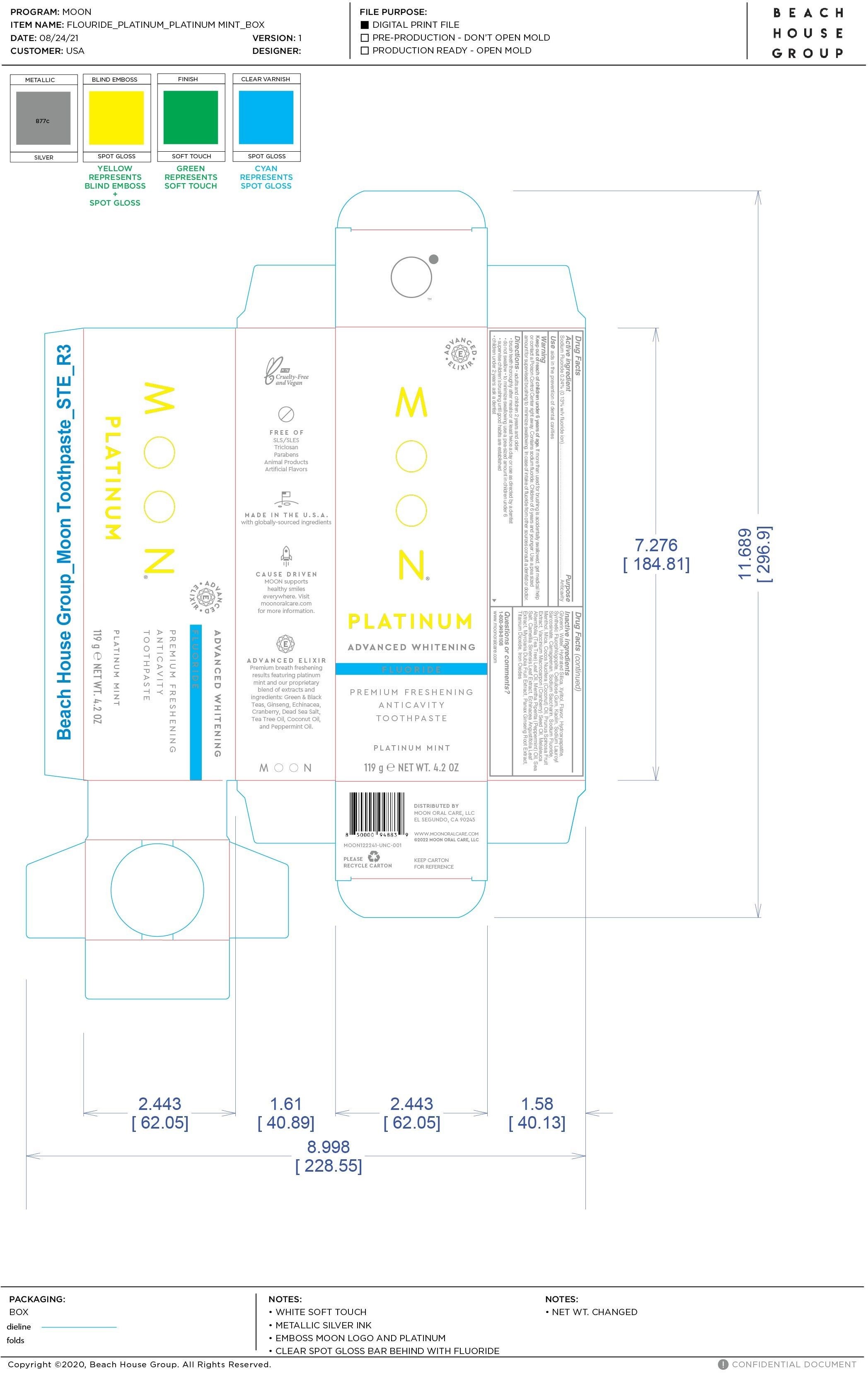 DRUG LABEL: Moon Platinum Advanced Whitening Anticavity
NDC: 82214-001 | Form: PASTE
Manufacturer: Moon Oral Care LLC
Category: otc | Type: HUMAN OTC DRUG LABEL
Date: 20260109

ACTIVE INGREDIENTS: SODIUM FLUORIDE 0.24 g/100 g
INACTIVE INGREDIENTS: CELLULOSE GUM; PROPYLENE GLYCOL; TEA TREE OIL; PEPPERMINT OIL; WATER; CARRAGEENAN; MAGNESIUM POTASSIUM ALUMINOSILICATE FLUORIDE; XYLITOL; TITANIUM DIOXIDE; MENTHOL; MICA; GLYCERIN; HYDRATED SILICA; KAOLIN; SODIUM LAUROYL SARCOSINATE; MYRCIARIA DUBIA FRUIT; ASIAN GINSENG; SACCHARIN SODIUM; COCONUT OIL; CRANBERRY SEED OIL; GREEN TEA LEAF; FERRIC OXIDE RED; SEA SALT; ECHINACEA ANGUSTIFOLIA LEAF; CAMELLIA SINENSIS LEAF OIL; GAULTHERIA PROCUMBENS (WINTERGREEN) LEAF OIL; LIMONENE, (+)-; SLOE; HYDROXYAPATITE; ETHYLHEXYLGLYCERIN; CAPRYLYL GLYCOL; SODIUM OLEOYL GLUTAMATE; PHENOXYETHANOL

Moon Platinum Advanced Whitening Anticavity Toothpaste

Active Ingredient Purpose

Sodium Fluoride 0.24% (0.13% w/v fluoride ion)

PURPOSE

Anticavity

INDICATIONS AND USAGE

Aids in the prevention of dental cavities.

Keep out of reach of children under 6 years of age.If more than than used for brushing is accidentally swallowed, get medical help or contact a Poison Control Center right away.

Contains Sodium Fluoride. In case of intake of flouride from other sources consult a dentist or doctor.

Children of 6 years and younger: Use a pea sized amount for supervised brushing to minimize swallowing. In case of intake of fluoride from other sources consult a dentist or doctor.

Keep out of reach of children under 6 years of age. If more than used for brushing is accidentally swallowed, get medical help or contact a Poison Control Center right away.

Directions

adults and children 2 years and older:

- brush teeth thoroughly after meals at least twice a day or use as directed by a dentist
- do not swallow
- to minimize swallowing, use a pea-sized amount in children under 6
- supervise children's brushing until good habits are established
- children under 2 years ask a dentist

Inactive ingredients

Glycerin, Water, Hydrated Silica, Xylitol, Faultheria Procumbens (Wintergreen) Leaf Oil, Hydroxyapatite, Synthetic Fluorophlogopite, Cellulose Gum, Mentha Piperita (Peppermint) Oil, Kaolin, Sodium Lauroyl Sarcosinate, Carrageenan, Flavor, Titanium Dioxide, Sodium Saccharin, Sodium Fluoride, Menthol, Caprylyl Glycol, Ethylhexylglycerin, Phenoxyethanol, Propylene Glycol, Sodium Olivoyl Glutamate, Mica, Limonene, Cocos Nucifera (Coconut) Oil, Prunus Spinosa Fruit Extract, Vaccinium Macrocarpon (Cranberry) Seed Oil, Iron Oxides, Melaleuca Alternifolia (Tea Tree) Leaf Oil, Sea Salt, Camellia Sinensis Leaf Extract, Echinacea Angustifolia Leaf Extract, Myciaria Dubia Fruit Extract, Panax Ginseng Root Extract

QUESTIONS

1(800) 949-8108

www.moonoralcare.com

DOSAGE AND ADMINISTRATION

Topical Paste

PACKAGE LABEL

Moon Platinum

Advanced Whitening

Fluoride

Premium Freshening

Anticavity Toothpaste

Platinum Mint

119 g Net Wt. 4.2 OZ